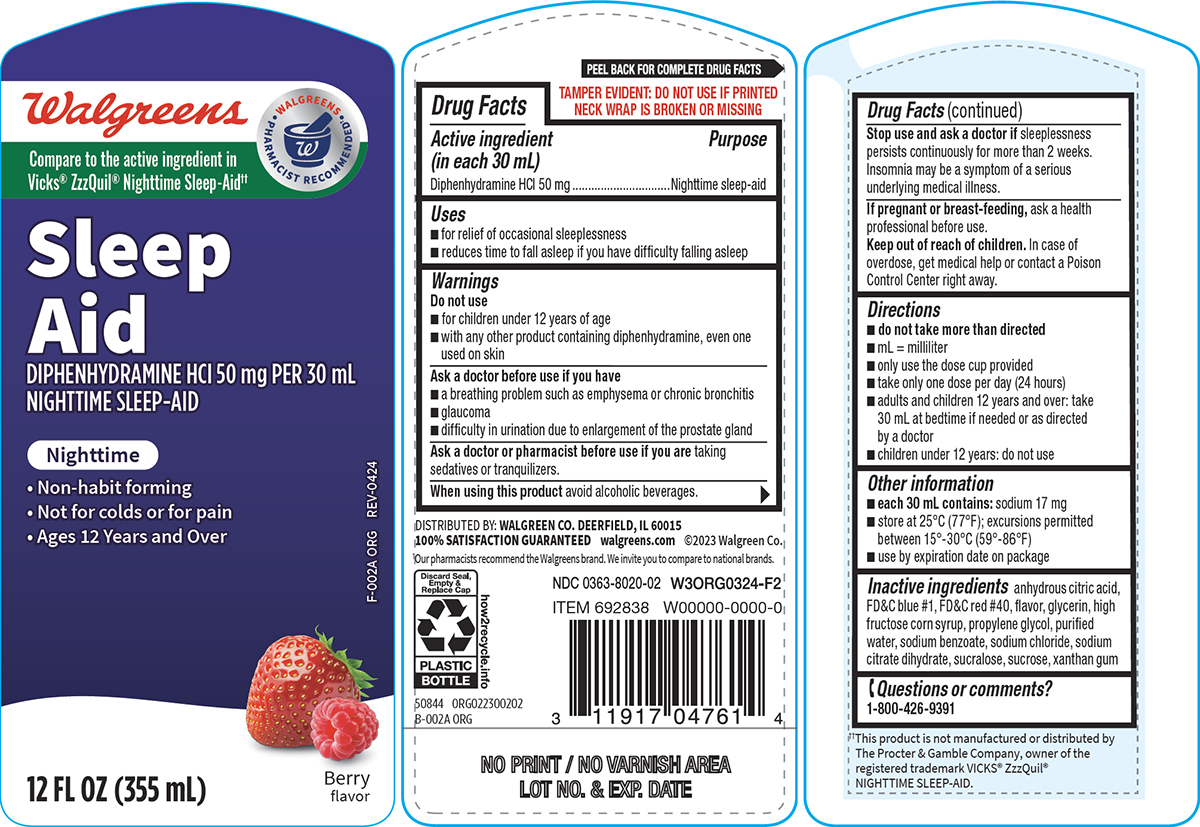 DRUG LABEL: Sleep Aid
NDC: 0363-8020 | Form: SOLUTION
Manufacturer: Walgreen Company
Category: otc | Type: HUMAN OTC DRUG LABEL
Date: 20250607

ACTIVE INGREDIENTS: DIPHENHYDRAMINE HYDROCHLORIDE 50 mg/30 mL
INACTIVE INGREDIENTS: ANHYDROUS CITRIC ACID; FD&C BLUE NO. 1; FD&C RED NO. 40; GLYCERIN; HIGH FRUCTOSE CORN SYRUP; PROPYLENE GLYCOL; WATER; SODIUM BENZOATE; SODIUM CHLORIDE; TRISODIUM CITRATE DIHYDRATE; SUCRALOSE; SUCROSE; XANTHAN GUM

Walgreens 44-002A-Sleep Aid

Active ingredient (in each 30 mL)

Diphenhydramine HCl 50 mg

Purpose

Nighttime sleep-aid

Uses

- for relief of occasional sleeplessness
- reduces time to fall asleep if you have difficulty falling asleep

Warnings

Do not use

- for children under 12 years of age
- with any other product containing diphenhydramine, even one used on skin

Ask a doctor before use if you have

- a breathing problem such as emphysema or chronic bronchitis
- glaucoma
- difficulty in urination due to enlargement of the prostate gland

Ask a doctor or pharmacist before use if you are

taking sedatives or tranquilizers.

When using this product

avoid alcoholic beverages.

Stop use and ask a doctor if

sleeplessness persists continuously for more than 2 weeks. Insomnia may be a symptom of a serious underlying medical illness.

If pregnant or breast-feeding,

ask a health professional before use.

Keep out of reach of children.

In case of overdose, get medical help or contact a Poison Control Center right away.

Directions

- do not take more than directed
- mL = milliliter
- only use the dose cup provided
- take only one dose per day (24 hours)
- adults and children 12 years and over: take 30 mL at bedtime if needed or as directed by a doctor
- children under 12 years: do not use

Other information

- each 30 mL contains: sodium 17 mg
- store at 25°C (77°F); excursions permitted between 15°-30°C (59°-86°F)
- use by expiration date on package

Inactive ingredients

anhydrous citric acid, FD&C blue #1, FD&C red #40, flavor, glycerin, high fructose corn syrup, propylene glycol, purified water, sodium benzoate, sodium chloride, sodium citrate dihydrate, sucralose, sucrose, xanthan gum

Questions or comments?

1-800-426-9391

Principal display panel

Walgreens

WALGREENS
PHARMACIST RECOMMENDED†

Compare to the active ingredient in
Vicks® ZzzQuil® Nighttime Sleep-Aid††

Sleep
Aid
DIPHENHYDRAMINE HCl 50 mg PER 30 mL
NIGHTTIME SLEEP-AID

Nighttime

• Non-habit forming
• Not for colds or for pain
• Ages 12 Years and Over

12 FL OZ (355 mL)

Berry
flavor

TAMPER EVIDENT: DO NOT USE IF PRINTED
NECK WRAP IS BROKEN OR MISSING

DISTRIBUTED BY: WALGREEN CO. DEERFIELD, IL 60015
100% SATISFACTION GUARANTEED walgreens.com ©2023 Walgreen Co.

†Our pharmacists recommend the Walgreens brand. We invite you to compare to national brands.

NDC 0363-8020-02

50844 ORG022300202

††This product is not manufactured or distributed by
The Procter & Gamble Company, owner of the
registered trademark VICKS® ZzzQuil®
NIGHTTIME SLEEP-AID.

Walgreens 44-002A